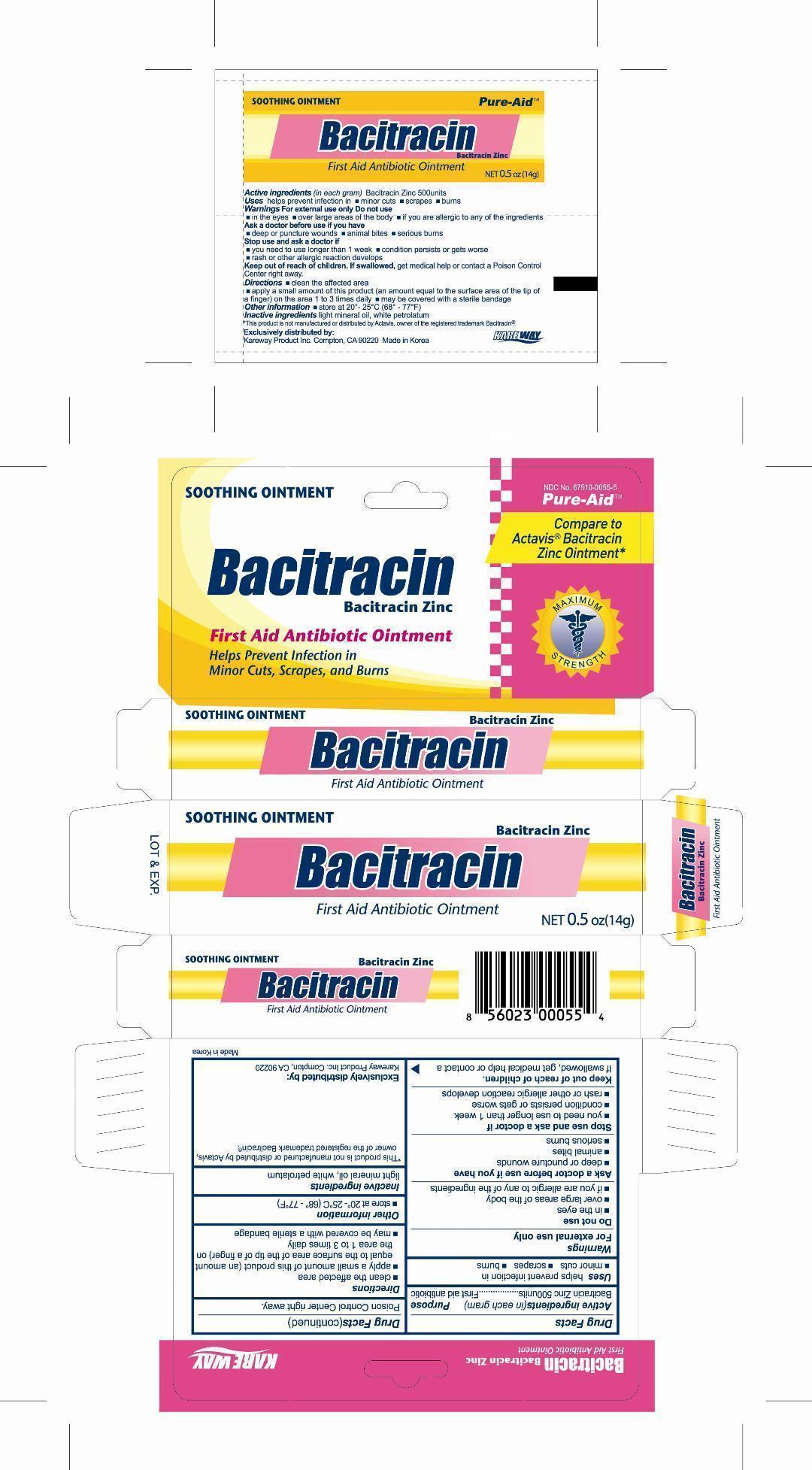 DRUG LABEL: Bacitracin Zinc
NDC: 67510-0055 | Form: OINTMENT
Manufacturer: Kareway Product, Inc.
Category: otc | Type: HUMAN OTC DRUG LABEL
Date: 20120716

ACTIVE INGREDIENTS: BACITRACIN ZINC 500 [USP'U]/1 g
INACTIVE INGREDIENTS: LIGHT MINERAL OIL; PETROLATUM

Drug Facts

Active ingredient (in each gram)

Bacitracin Zinc 500 units

Purpose

First aid antibiotic

Uses

helps prevent infection in

- minor cuts
- scrapes
- burns

Warnings

For external use only

Do not use

- in the eyes
- over large areas of the body
- if you are allergic to any of the ingredients

Ask a doctor before use if you have

- deep or puncture wounds
- animal bites
- serious burns

Stop use and ask a doctor if

- you need to use longer than 1 week
- condition persists or gets worse
- rash or other allergic reaction develops

Keep out of reach of children

If swallowed, get medical help or contact a Poison Control Center right away.

Directions

- clean the affected area
- apply a small amount of this product (an amount equal to the surface area of the tip of a finger) on the area 1 to 3 times daily
- may be covered with a sterile bandage

Other information

- store at 20 - 25C (68 - 77F)

Inactive ingredients

light mineral oil, white petrolatum

Package label

Bacitracin Zinc Ointment